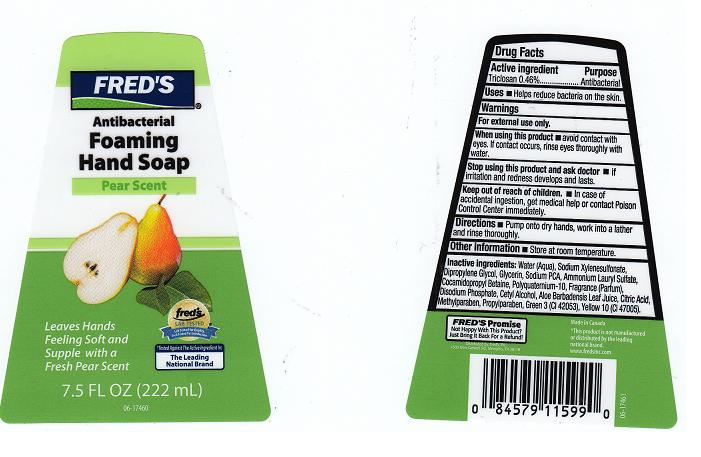 DRUG LABEL: ANTIBACTERIAL FOAMING 
NDC: 55315-184 | Form: LIQUID
Manufacturer: FRED'S INC
Category: otc | Type: HUMAN OTC DRUG LABEL
Date: 20110708

ACTIVE INGREDIENTS: TRICLOSAN 0.46 mL/100 mL
INACTIVE INGREDIENTS: WATER; SODIUM XYLENESULFONATE; DIPROPYLENE GLYCOL; GLYCERIN; SODIUM PYRROLIDONE CARBOXYLATE; AMMONIUM LAURYL SULFATE; COCAMIDOPROPYL BETAINE; POLYQUATERNIUM-10 (400 CPS AT 2%); SODIUM PHOSPHATE, DIBASIC, DIHYDRATE; CETYL ALCOHOL; ALOE VERA LEAF; CITRIC ACID MONOHYDRATE; METHYLPARABEN; PROPYLPARABEN; FD&C GREEN NO. 3; D&C YELLOW NO. 10

DRUG FACTS

Active Ingredient

Triclosan 0.46%

Purpose

Antibacterial

Uses

For washing to decrease bacteria on the skin.

Warnings

For external use only.

When using this product

Avoid contact with eyes. If contact occurs, rinse with water.

Stop using this product and ask doctor if

Irritation or redness develops and lasts.

Keep out of reach of children

In case of accidental ingestion, get medical help and contact a Poison Control Center immediately.

Directions

Pump onto dry hands, work into a lather. Rinse thoroughly.

Questions or Comments

1-866-322-2439

Inactive Ingredients

WATER, SODIUM XYLENE SULFONATE, DIPROPYLENE GLYCOL, GLYCERIN, SODIUM PCA, AMMONIUM LAURYL SULFATE, COCAMIDOPROPYL BETAINE, POLYQUATERNIUM-10, FRAGRANCE, DISODIUM PHOSPHATE, CETYL ALCOHOL, ALOE BARBADENSIS LEAF JUICE, CITRIC ACID, METHYLPARABEN, PROPYLPARABEN, GREEN 3 (CI 42053), YELLOW 10 (CI 47005).